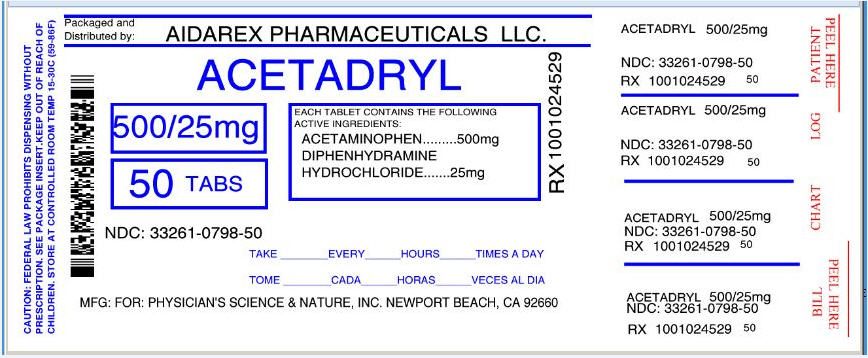 DRUG LABEL: Acetadryl
NDC: 33261-798 | Form: TABLET, FILM COATED
Manufacturer: Aidarex Pharmaceuticals LLC
Category: otc | Type: HUMAN OTC DRUG LABEL
Date: 20131112

ACTIVE INGREDIENTS: ACETAMINOPHEN 500 mg/1 1; DIPHENHYDRAMINE HYDROCHLORIDE 25 mg/1 1
INACTIVE INGREDIENTS: CROSCARMELLOSE SODIUM; CROSPOVIDONE; FD&C BLUE NO. 1; HYDROXYPROPYL CELLULOSE (TYPE H); HYPROMELLOSE 2208 (100 MPA.S); MAGNESIUM STEARATE; CELLULOSE, MICROCRYSTALLINE; POVIDONES; STARCH, CORN; PROPYLENE GLYCOL; SODIUM STARCH GLYCOLATE TYPE A POTATO; STEARIC ACID; TITANIUM DIOXIDE; SILICON DIOXIDE

Acetadryl™ Pain Reliever/Sleep Aid

Active ingredients

Acetaminophen 500 mg and Diphenhydramine HCl 25 mg

Purpose

Pain Reliever/Nightime Sleep Aid

Uses

Temporary relief of occasional headaches and minor aches and pains with accompanying sleeplessness.

Warnings

Liver warning: This product contains acetaminophen. Severe liver damage may occur if you take

- more than 2 caplets in 24 hours, which is the maximum daily amount for this product
- with other drugs containing acetaminophen
- 3 or more alcoholic drinks every day while using this product

Do not use

- with any other drug containing acetaminophen (prescription or nonprescription). If you are not sure whether a drug contains acetaminophen, ask a doctor or pharmacist.
- in children under 12 years of age
- with any other product containing diphenhydramine, even one used on skin
- if you are allergic to acetaminophen or any of the inactive ingredients in this product

Ask a doctor before use if you have

- liver disease
- a breathing problem such as emphysema or chronic bronchitis
- difficulty in urination due to enlargement of the prostate gland
- glaucoma

Ask a doctor or pharmacist before use if you are

- taking the blood thinning drug warfarin
- taking sedatives or tranquilizers

When using this product

- drowsiness will occur
- avoid alcoholic drinks
- do not drive a motor vehicle or operate machinery

Stop use and ask a doctor if

- sleeplessness persists continuously for more than 2 weeks. Insomnia may be a symptom of a serious underlying medical illness.
- pain gets worse or lasts more than 10 days
- fever gets worse or lasts more than 3 days
- new symptoms occur
- redness or swelling is present

These could be signs of a serious condition.

If pregnant or breast-feeding,

ask a health professional before use.

Overdose warning:

Taking more than the recommended dose (overdose) may cause liver damage. In case of overdose, get medical help or contact a Poison Control Center right away. (1-800-222-1222). Quick medical attention is critical for adults as well as for children even if you do not notice any signs or symptoms.

Directions

Do not take more than directed (see overdose warning)

Adults and children 12 years of age or over:

- Take 2 caplets at bedtime if needed, or as directed by a doctor

Children under 12 years: Do not use this adult product in children under 12 years of age; this will provide more than the recommended dose (overdose) and may cause liver damage.

Other information

- Store at room temperature

Inactive ingredients

Croscarmellose Sodium, Crospovidone, FD&C Blue #1, Hydroxypropyl Cellulose, Hypromellose, Magnesium Stearate, Microcrystalline Cellulose, Povidone, Pregelatinized Starch, Propylene Glycol, Silica, Sodium Starch Glycolate, Stearic Acid and Titanium Dioxide.

Questions or comments?

If you have any questions or comments, or to report an adverse event, please contact: Physician's Science and Nature Inc.

714-875-6316

Manufactured for:

Physician's Science and Nature Inc.

220 Newport Center Drive 11-634

Newport Beach, CA 92660

Repackaged By :
Aidarex Pharmaceuticals LLC,
Corona, CA 92880